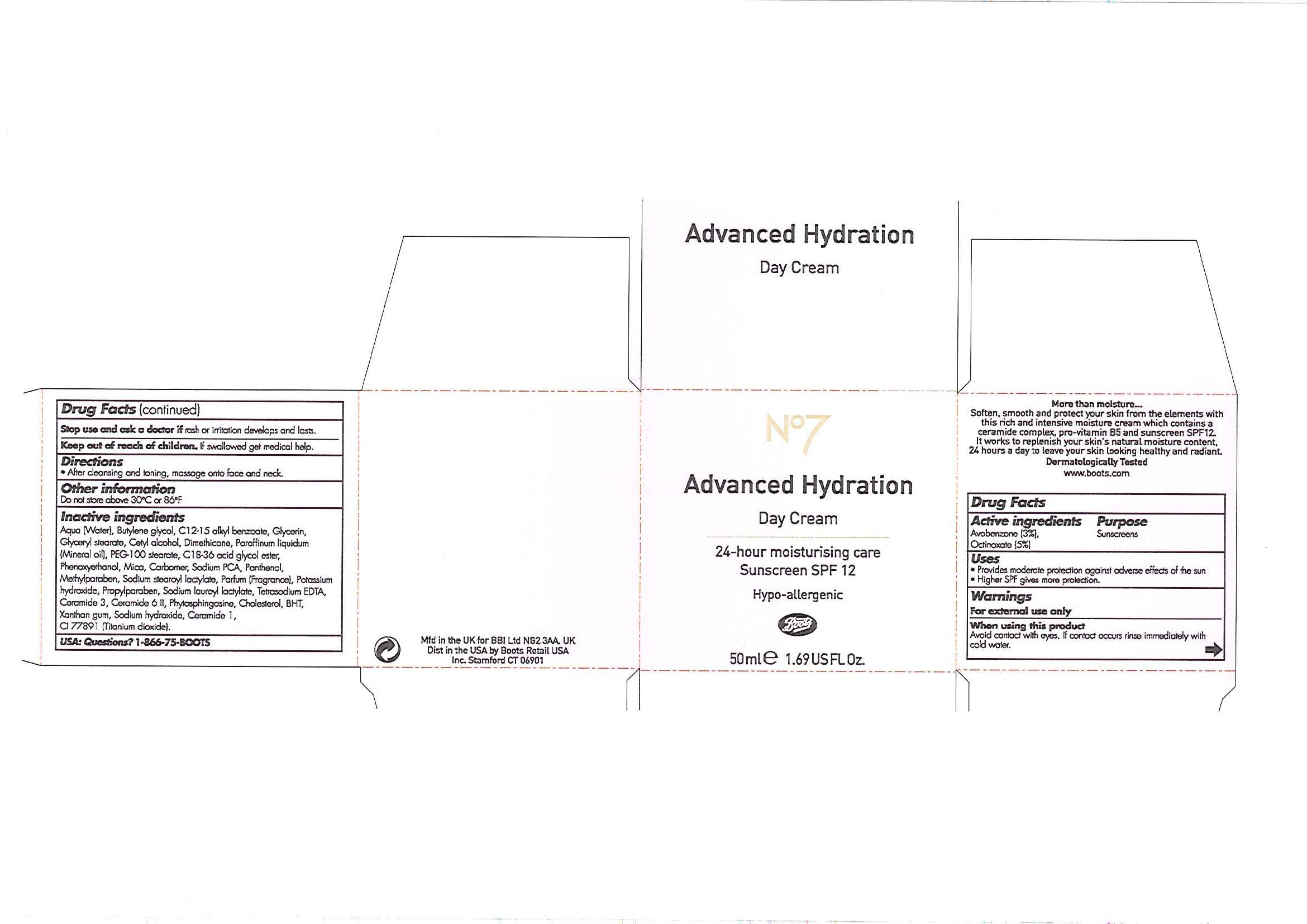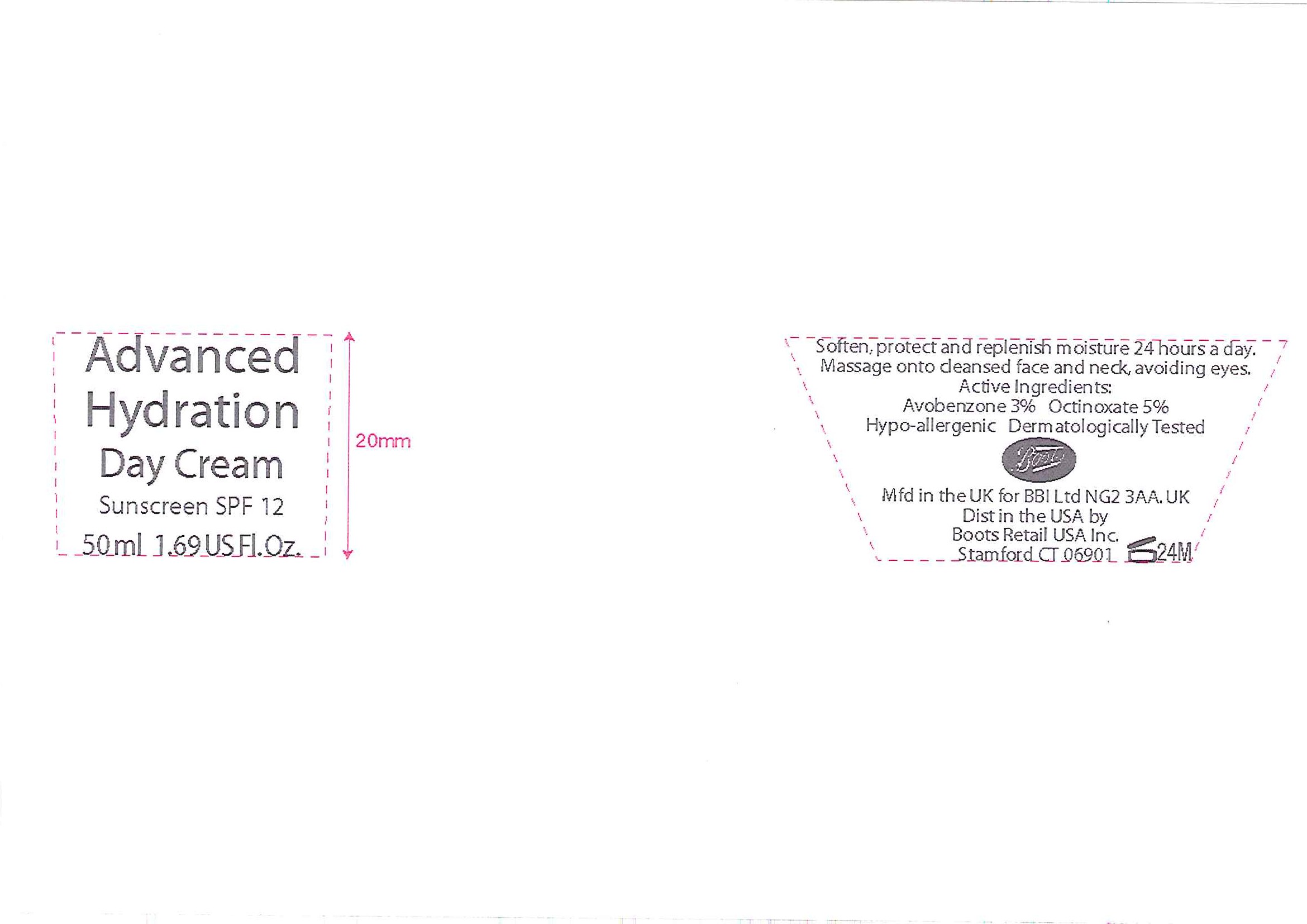 DRUG LABEL: No7 Advanced Hydration Day Sunscreen SPF 12
NDC: 11489-061 | Form: CREAM
Manufacturer: BCM Ltd
Category: otc | Type: HUMAN OTC DRUG LABEL
Date: 20101206

ACTIVE INGREDIENTS: OCTINOXATE 2.5 mL/50 mL; AVOBENZONE 1.5 mL/50 mL
INACTIVE INGREDIENTS: WATER; BUTYLENE GLYCOL; GLYCERIN; GLYCERYL MONOSTEARATE; CETYL ALCOHOL; DIMETHICONE; LIGHT MINERAL OIL; POLYOXYL 100 STEARATE; PHENOXYETHANOL; CARBOMER HOMOPOLYMER TYPE C; SODIUM PYRROLIDONE CARBOXYLATE; PANTHENOL; METHYLPARABEN; POTASSIUM HYDROXIDE; PROPYLPARABEN; CHOLESTEROL; BUTYLATED HYDROXYTOLUENE; XANTHAN GUM; SODIUM HYDROXIDE; TITANIUM DIOXIDE

Carton and jar labels

ACTIVE INGREDIENT

No7 Advanced Hydration Day Cream Sunscreen SPF 12

Active Ingredients Purpose

Avobenzone (3%) Sunscreens

Octinoxate (5%)

PURPOSE

- Provides moderate protection against adverse effects of the sun
- Higher SPF gives more protection

Warnings

For external use only

When using this product

Avoid contact with eyes. If contact occurs rinse immediately with cold water.

Stop use and ask a doctor if rash or irritation develops and lasts.

Keep out of reach of children. If swallowed get medical help.

Directions

After cleansing and toning, massage onto face and neck.

Other information

- Do not store above 30^0C or 86^0F

Inactive ingredients

Aqua (Water), Butylene glycol, C12-15 alkyl benzoate, Glycerin, Glyceryl stearate, Cetyl alcohol, Dimethicone, Paraffinum liquidum (Mineral oil), PEG-100 stearate, C18-36 acid glycol ester, Phenoxyethanol, Mica, Carbomer, Sodium PCA, Panthenol, Methylparaben, Sodium stearoyl lactylate, Parfum (Fragrance), Potassium hydroxide, Propylparaben, Sodium lauroyl lactylate, Tetrasodium EDTA, Ceramide 3, Ceramide 6 II, Phytosphingosine, Cholesterol, BHT, Xanthan gum, Sodium hydroxide, Ceramide 1, CI 77891 (Titanium dioxide).

USA: Questions? 1-866-75-BOOTS

PATIENT COUNSELING INFORMATION

Mfd in the UK for BBI Ltd NG2 3AA. UK

Dist in the USA by Boots Retail USA Inc. Stamford CT 06901

DESCRIPTION

Jar label

Soften, protect and replenish moisture 24 hours a day.

Massage onto cleansed face and neck, avoiding eyes.

Hypo-allergenic Dermatologically Tested

Active Ingredients

Avobenzone 3%

Octinoxate 5%

PATIENT COUNSELING INFORMATION

Boots

Mfd in the UK for BBI Ltd NG2 3AA. UK

Dist in the USA by Boots Retail USA Inc. Stamford CT 06901

Carton label

No7 Advanced Hydration

Day Cream

24 hour moisturising care

Hypo-allergenic

Boots

50ml e 1.69 US Fl. Oz

Advanced Hydration Day Cream carton.jpg

Jar label

Advanced Hydration Day Cream

Sunscreen SPF 12

50ml 1.69 US Fl. Oz

Advanced Hydration Day Cream jar.jpg